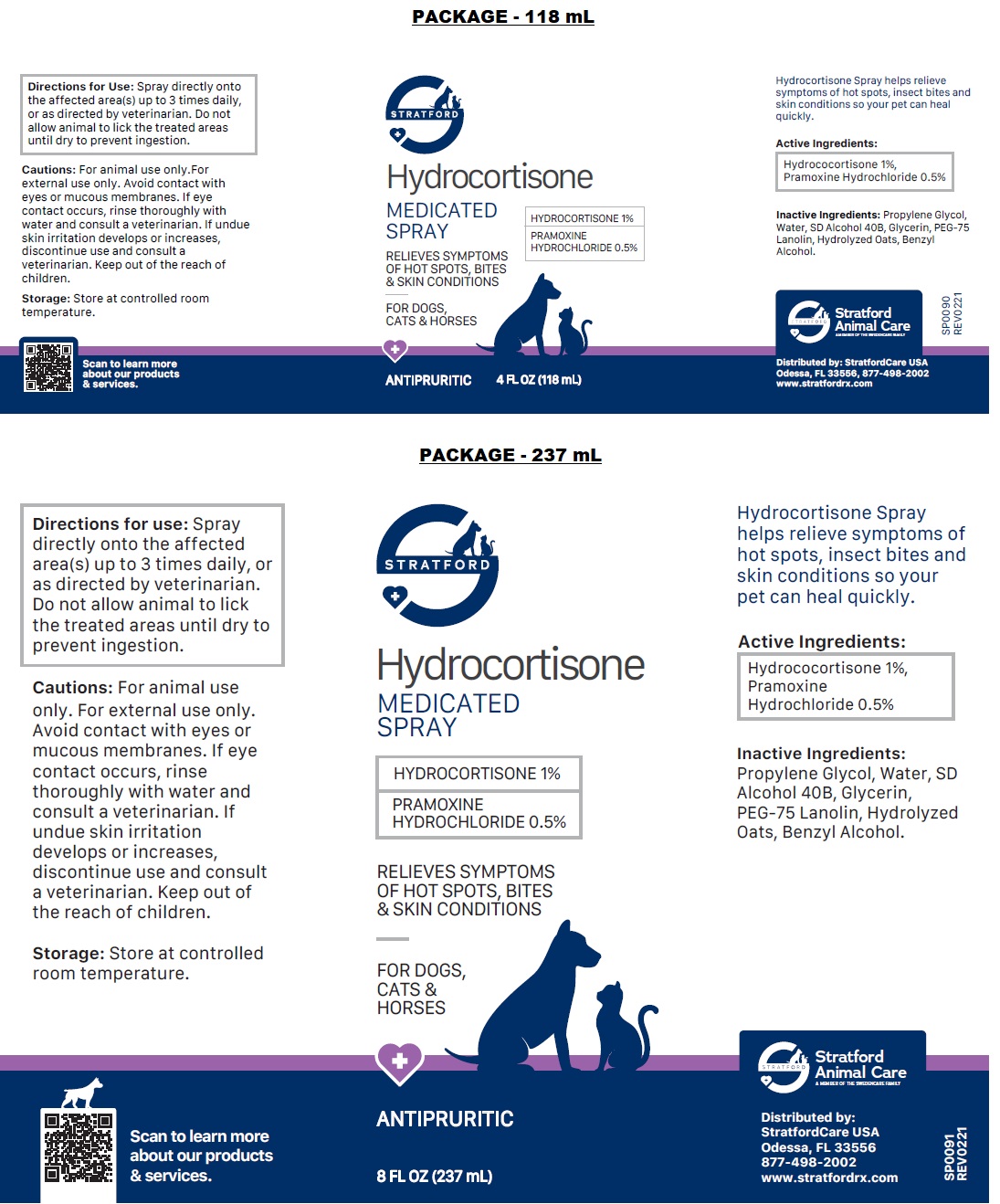 DRUG LABEL: Hydrocortisone
NDC: 86069-120 | Form: SPRAY
Manufacturer: Stratford Care Usa, Inc.
Category: animal | Type: OTC ANIMAL DRUG LABEL
Date: 20221122

ACTIVE INGREDIENTS: HYDROCORTISONE 1 g/100 mL; PRAMOXINE HYDROCHLORIDE 0.5 g/100 mL
INACTIVE INGREDIENTS: PROPYLENE GLYCOL; WATER; ALCOHOL; GLYCERIN; PEG-75 LANOLIN; OAT; BENZYL ALCOHOL

Hydrocortisone MEDICATED SPRAY

Active Ingredients:

Hydrocortisone 1%,
Pramoxine Hydrochloride 0.5%

PURPOSE

ANTIPRURITIC

INDICATIONS AND USAGE

Hydrocortisone Spray helps relieve symptoms of hot spots, insect bites and skin conditions so your pet can heal quickly.

INACTIVE INGREDIENT

Inactive Ingredients: Propylene Glycol, Water, SD Alcohol 40B, Glycerin, PEG-75 Lanolin, Hydrolyzed Oats, Benzyl Alcohol.

DOSAGE AND ADMINISTRATION

Directions for Use: Spray directly onto the affected area(s) up to 3 times daily, or as directed by veterinarian. Do not allow animal to lick the treated areas until dry to prevent ingestion.

PRECAUTIONS

Cautions: For animal use only. For external use only. Avoid contact with eyes or mucous membranes. If eye contact occurs, rinse thoroughly with water and consult a veterinarian. If undue skin irritation develops or increases, discontinue use and consult a veterinarian. Keep out of the reach of children.

Storage: Store at controlled room temperature.

MEDICATED SPRAY

RELIEVES SYMPTOMS OF HOT SPOTS, BITES & SKIN CONDITIONS

FOR DOGS, CATS & HORSES

Stratford Animal Care
A MEMBER OF THE SWEDENCARE FAMILY

Distributed by:
StratfordCare USA
Odessa, FL 33556
877-498-2002
www.stratfordrx.com